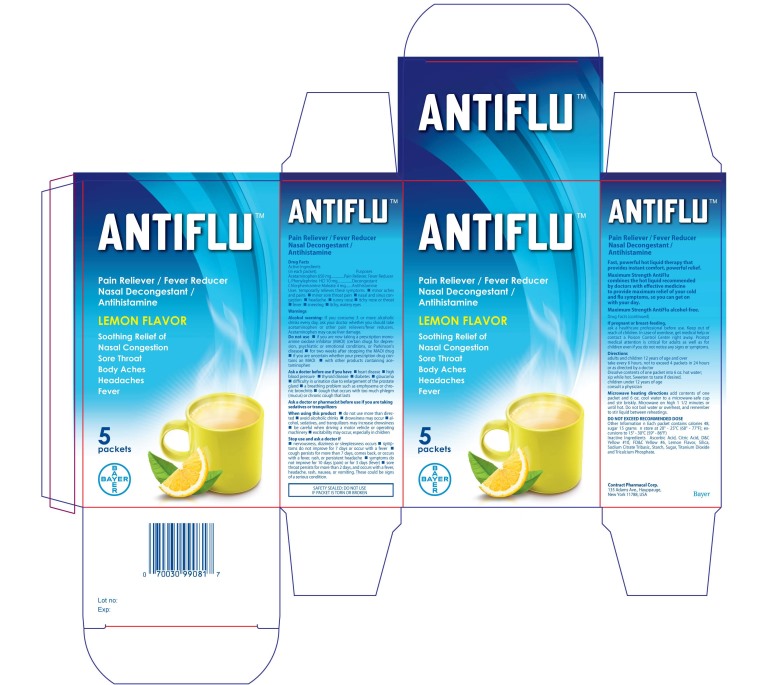 DRUG LABEL: Antiflu
NDC: 0280-0045 | Form: POWDER, FOR SOLUTION
Manufacturer: Bayer HealthCare LLC.
Category: otc | Type: HUMAN OTC DRUG LABEL
Date: 20250117

ACTIVE INGREDIENTS: PHENYLEPHRINE HYDROCHLORIDE 10 mg/17000 mg; ACETAMINOPHEN 650 mg/17000 mg; CHLORPHENIRAMINE MALEATE 4 mg/17000 mg
INACTIVE INGREDIENTS: ASCORBIC ACID; CITRIC ACID MONOHYDRATE; D&C YELLOW NO. 10

Antiflu Powder Pouches